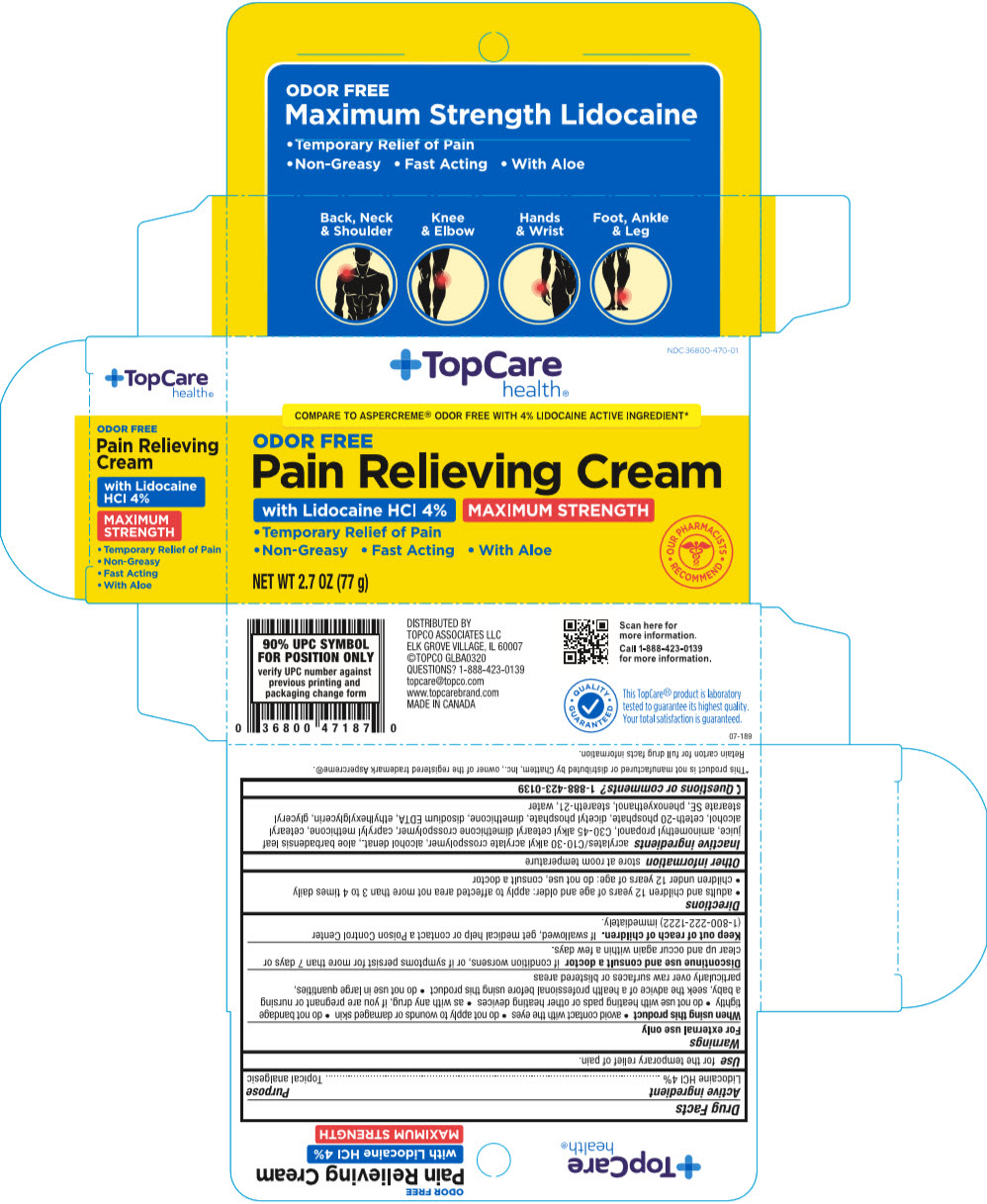 DRUG LABEL: TopCare Pain Relieving
NDC: 36800-470 | Form: CREAM
Manufacturer: Topco Associates LLC
Category: otc | Type: HUMAN OTC DRUG LABEL
Date: 20241105

ACTIVE INGREDIENTS: LIDOCAINE HYDROCHLORIDE 40 mg/1 g
INACTIVE INGREDIENTS: CARBOMER INTERPOLYMER TYPE A (ALLYL SUCROSE CROSSLINKED); Alcohol; ALOE VERA LEAF; Aminomethylpropanol; Caprylyl Trisiloxane; Cetostearyl Alcohol; Ceteth-20 Phosphate; Dihexadecyl Phosphate; Dimethicone; EDETATE DISODIUM; Ethylhexylglycerin; Glyceryl Stearate SE; Phenoxyethanol; Steareth-21; Water

TopCare Pain Relieving Cream
Topical Analgesic

Drug Facts

Active ingredient

Lidocaine HCl 4%

Purpose

Topical analgesic

Uses

for the temporary relief of pain.

Warnings

For external use only

When using this product

- avoid contact with eyes
- do not apply to wounds or damaged skin
- do not bandage tightly
- do not use with heating pads or other heating devices
- as with any drug, if you are pregnant or nursing a baby, seek the advice of a health professional before using this product
- do not use in large quantities, particularly over raw surfaces or blistered areas

STOP USE

Discontinue use and consult a doctor if condition worsens, or if symptoms persist for more than 7 days or clear up and occur again within a few days.

Keep out of reach of children. If swallowed, get medical help or contact a Poison Control Center (1-800-222-1222) immediately.

Directions

- adults and children 12 years of age and older: apply to affected area not more than 3 to 4 times daily
- children under 12 years of age: do not use, consult a doctor

Other information

store at room temperature

Inactive ingredients

Acrylates/C10-30 Alkyl Acrylate Crosspolymer, Alcohol denat., Aloe Barbadensis Leaf Juice, Aminomethyl Propanol, C30-45 Alkyl Cetearyl Dimethicone Crosspolymer, Caprylyl Methicone, Cetearyl Alcohol, Ceteth-20 Phosphate, Dicetyl Phosphate, Dimethicone, Disodium EDTA, Ethylhexylglycerin, Glyceryl Stearare SE, Phenoxyethanol, Steareth-21, Water.

Questions or comments?

1-888-423-0139

DISTRIBUTED BY
TOPCO ASSOCIATES LLC
ELK GROVE VILLAGE, IL 60007

PRINCIPAL DISPLAY PANEL - 77 g Bottle Carton

NDC 36800-470-01

TopCare
health®

COMPARE TO ASPERCREME® ODOR FREE WITH 4% LIDOCAINE ACTIVE INGREDIENT*

ODOR FREE
Pain Relieving Cream
with Lidocaine HCl 4%
MAXIMUM STRENGTH
•Temporary Relief of Pain
•Non-Greasy •Fast Acting •With Aloe

NET WT 2.7 OZ (77 g)

• OUR PHARMACISTS •
RECOMMEND